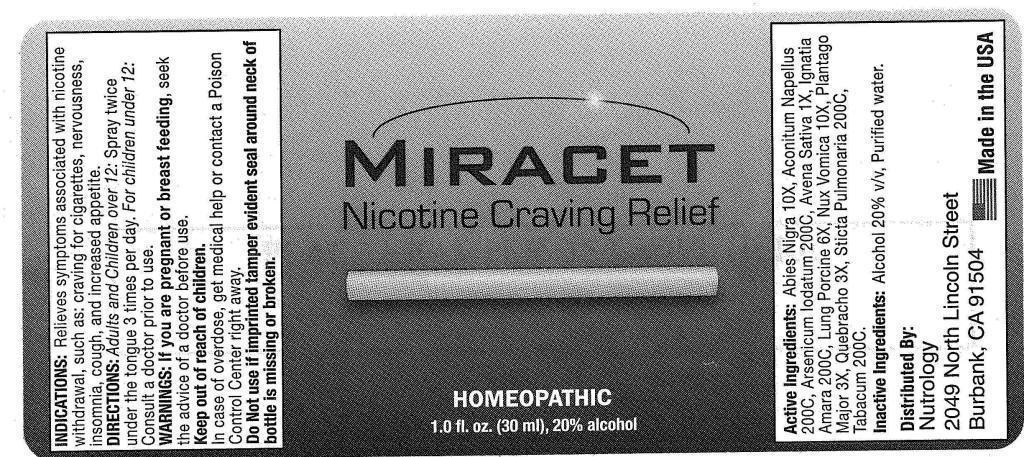 DRUG LABEL: Miracet
NDC: 43695-0004 | Form: LIQUID
Manufacturer: Pacific Naturals
Category: homeopathic | Type: HUMAN OTC DRUG LABEL
Date: 20130801

ACTIVE INGREDIENTS: PICEA MARIANA RESIN 10 [hp_X]/1 mL; ACONITUM NAPELLUS 200 [hp_C]/1 mL; ARSENIC TRIIODIDE 200 [hp_C]/1 mL; AVENA SATIVA FLOWERING TOP 1 [hp_X]/1 mL; STRYCHNOS IGNATII SEED 200 [hp_C]/1 mL; SUS SCROFA LUNG 6 [hp_X]/1 mL; STRYCHNOS NUX-VOMICA SEED 10 [hp_X]/1 mL; PLANTAGO MAJOR 3 [hp_X]/1 mL; ASPIDOSPERMA QUEBRACHO-BLANCO BARK 3 [hp_X]/1 mL; LOBARIA PULMONARIA 200 [hp_C]/1 mL; TOBACCO LEAF 200 [hp_C]/1 mL
INACTIVE INGREDIENTS: WATER; ALCOHOL

DRUG FACTS:

ACTIVE INGREDIENTS:

Abies Nigra 10X, Aconitum Napellus 200C, Arsenicum Iodatum 200C, Avena Sativa 1X, Ignatia Amara 200C, Lung Suis 6X, Nux Vomica 10X, Plantago Major 3X, Quebracho 3X, Stricta Pulmonaria 200C, Tabacum 200C.

INDICATIONS:

Relieves symptoms associated with nicotine withdrawal, such as: craving for cigarettes, nervousness, insomnia, cough, and increased appetite.

WARNINGS:

If you are pregnant or breast feeding, seek the advice of a doctor before use.

Keep out of reach of children.

In case of overdose, get medical help or contact a Poison Control Center right away.

Do Not use if imprinted tamper evident seal around neck of bottle is missing or broken.

DIRECTIONS:

Adults and Children over 12: Spray twice under the tongue 3 times per day.

For Children under 12: Consult a doctor prior to use.

INACTIVE INGREDIENTS:

Alcohol 20% v/v, Purified water.

Keep out of reach of children. In case of overdose, get medical help or contact a Poison Control Center right away.

INDICATIONS:

Relieves symptoms associated with nicotine withdrawal, such as: craving for cigarettes, nervousness, insomnia, cough, and increased appetite.

QUESTIONS:

Distributed By:

Nutrology

2049 North Lincoln Street

Burbank, CA 91504

PACKAGE DISPLAY LABEL:

MIRACET

Nicotine Craving Relief

HOMEOPATHIC

1.0 fl. oz. (30 mL), 20% alcohol